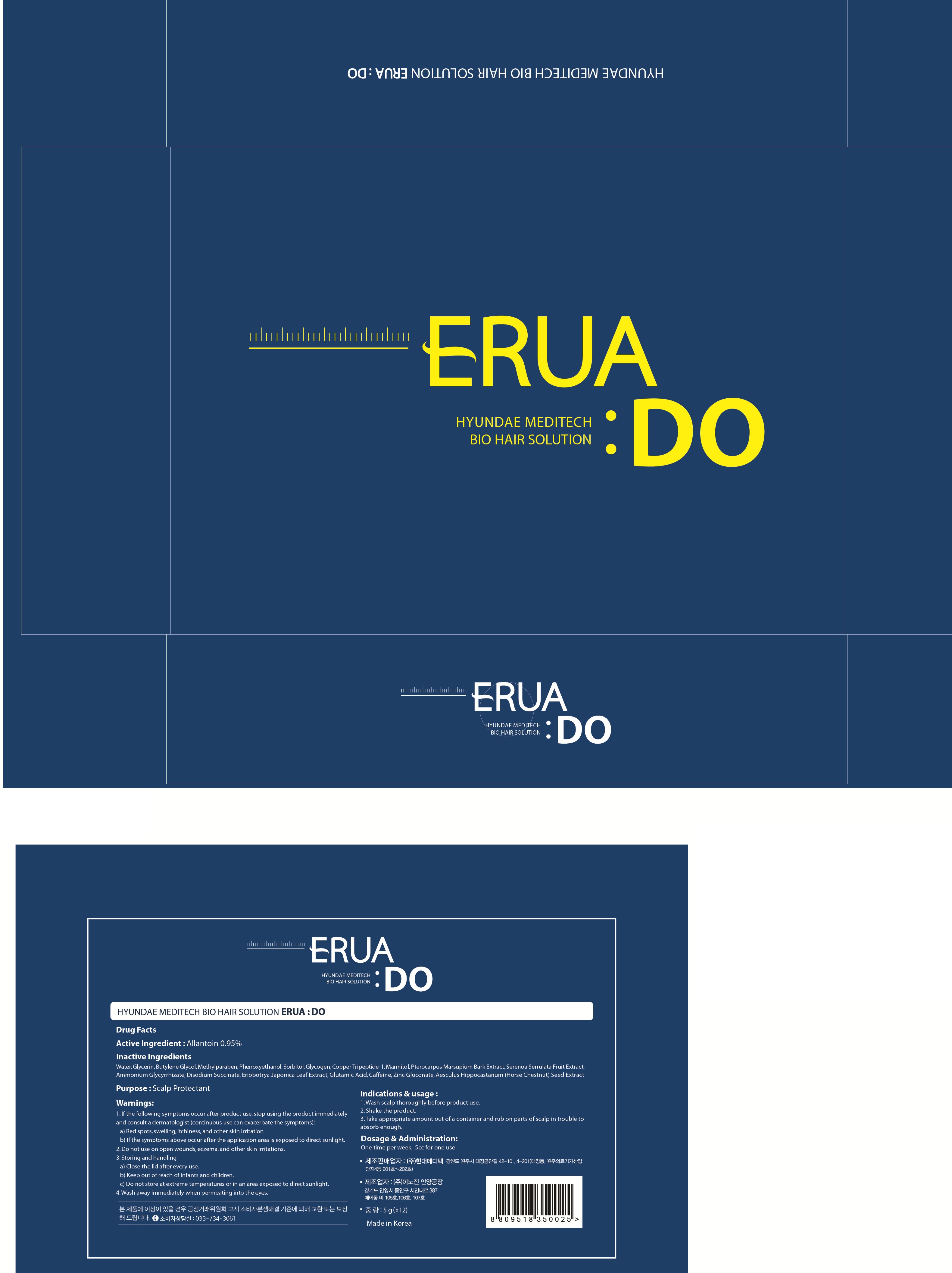 DRUG LABEL: HYUNDAE MEDITECH BIO HAIR SOLU TION ERUA DO
NDC: 70540-030 | Form: SOLUTION
Manufacturer: INNOGENE CO.,LTD
Category: otc | Type: HUMAN OTC DRUG LABEL
Date: 20161005

ACTIVE INGREDIENTS: Allantoin 0.04 g/5 g
INACTIVE INGREDIENTS: Water; Glycerin

ACTIVE INGREDIENT

Active Ingredient: Allantoin 0.95%

INACTIVE INGREDIENT

Inactive Ingredients: Water, Glycerin, Butylene Glycol, Methylparaben, Phenoxyethanol, Sorbitol, Glycogen, Copper Tripeptide-1, Mannitol, Pterocarpus Marsupium Bark Extract, Serenoa Serrulata Fruit Extract, Ammonium Glycyrrhizate, Disodium Succinate, Eriobotrya Japonica Leaf Extract, Glutamic Acid, Caffeine, Zinc Gluconate, Aesculus Hippocastanum (Horse Chestnut) Seed Extract

PURPOSE

Purpose: Scalp Protectant

WARNINGS

Warnings: 1. If the following symptoms occur after product use, stop using the product immediately and consult a dermatologist (continuous use can exacerbate the symptoms): a) Red spots, swelling, itchiness, and other skin irritation b) If the symptoms above occur after the application area is exposed to direct sunlight. 2. Do not use on open wounds, eczema, and other skin irritations. 3. Storing and handling a) Close the lid after every use. b) Keep out of reach of infants and children. c) Do not store at extreme temperatures or in an area exposed to direct sunlight. 4. Wash away immediately when permeating into the eyes.

KEEP OUT OF REACH OF CHILDREN

Keep out of reach of infants and children.

INDICATIONS & USAGE

Indications & usage: 1. Wash scalp tholoughly before product use. 2. Shake the product. 3. Take appropriate amount out of a container and rub on parts of scalp in trouble to absorb enough.

DOSAGE & ADMINISTRATION

Dosage & Administration: One time per week, 5cc for one use